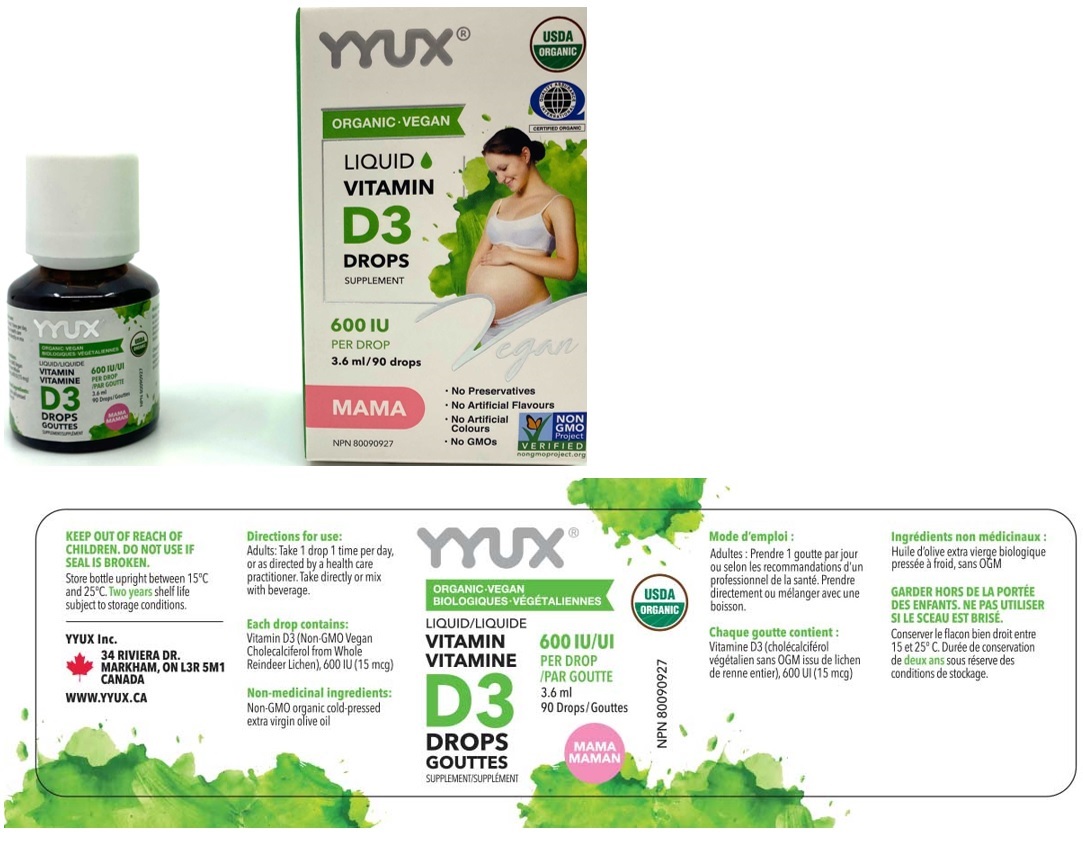 DRUG LABEL: YYUX Vegan Mama Liquid Vitamin D3 Drops 600 IU
NDC: 81303-560 | Form: SOLUTION/ DROPS
Manufacturer: Yyux Inc
Category: other | Type: DIETARY SUPPLEMENT
Date: 20201229

ACTIVE INGREDIENTS: CHOLECALCIFEROL 15 ug/0.04 mL
INACTIVE INGREDIENTS: OLIVE OIL

YYUX® ORGANIC-VEGAN LIQUID VITAMIN D3 DROPS SUPPLEMENT

Active Ingredient

Vitamin D3 (Cholecalciferol) 600IU (15ug per drop)

Supplement Facts; Serving Size: 1 drop; Serving Per Container: 90
Amount Per Serving | DV%
Calories 0
Total Fat 0 g | <1%
Cholesterol 0 mg | 0%
Vitamin D3 (Cholecalciferol) 15mcg (600IU) | 100%
Other ingredients: Olive Oil

Non-medicinal ingredients: Non-GMO organic cold-pressed extra virgin olive oil

Warnings:

KEEP OUT OF REACH OF CHILDREN. DO NOT USE IF SEAL IS BROKEN.

Storage:

Store bottle upright between 15°C and 25°C. Two years shelf life subject to storage conditions.

Directions for use:

Adults: Take 1 drop 1 time per day, or as directed by a health care practitioner. Take directly or mix with beverage.

A dropper supplied.

HEALTH CLAIM

Helps in the development and maintenance of bones and teeth. Helps in the absorption and use of calcium and phosphorus. Helps with immune function.

Each drop contains: Vitamin D3 (Non-GMO Vegan Cholecalciferol from Whole Reindeer Lichen), 600 IU (15 mcg)

USDA ORGANIC

QUALITY ASSURANCE INTERNATIONAL

CERTIFIED ORGANIC

NON GMO Project VERIFIED

nongmoproject.org

• No Preservatives

• No Artificial Flavours

• No Artificial Colours

• No GMOs
YYUX Inc.
34 RIVIERA DR.
MARKHAM, ON L3R 5M1
CANADA
WWW.YYUX.CA